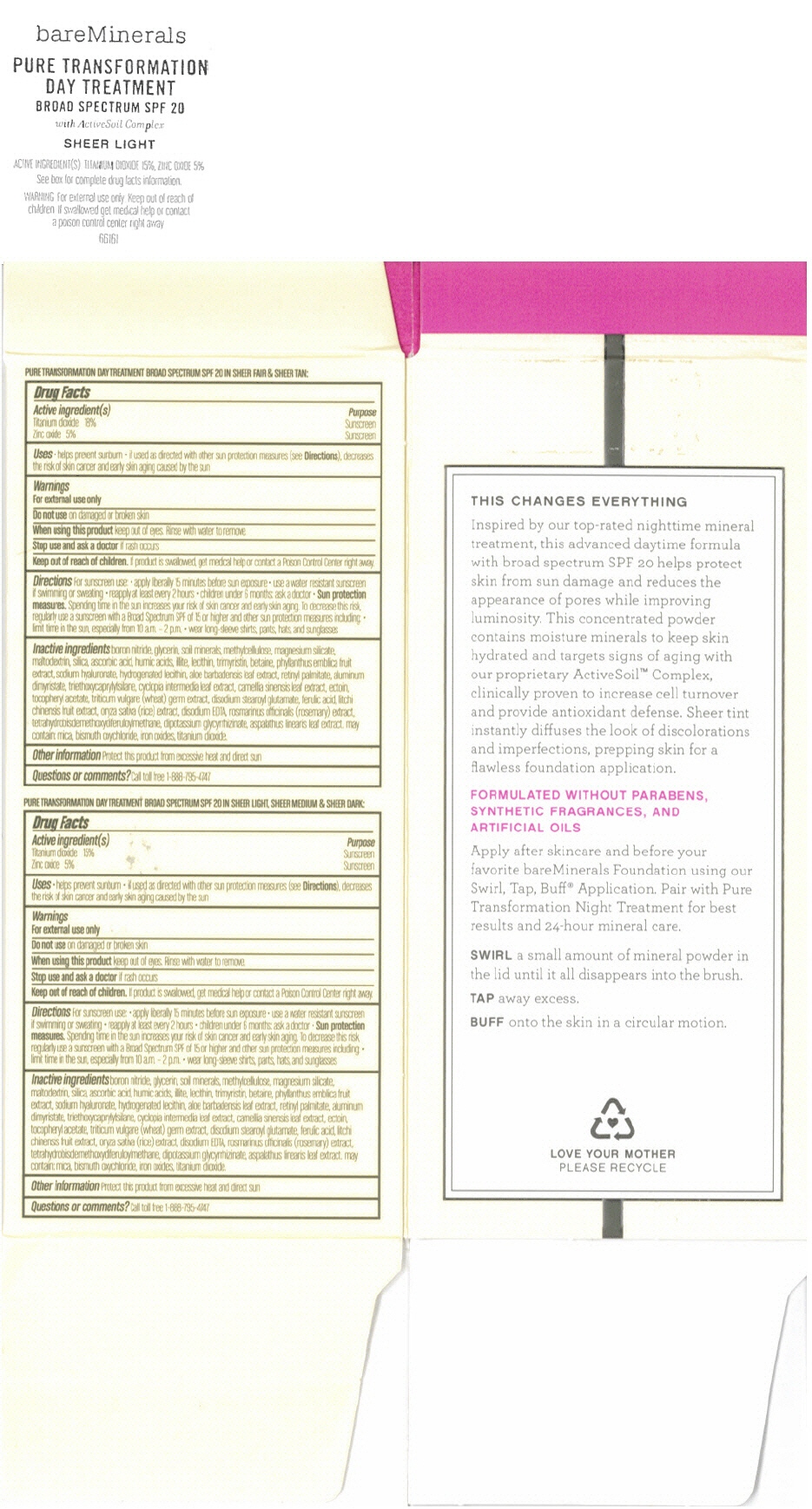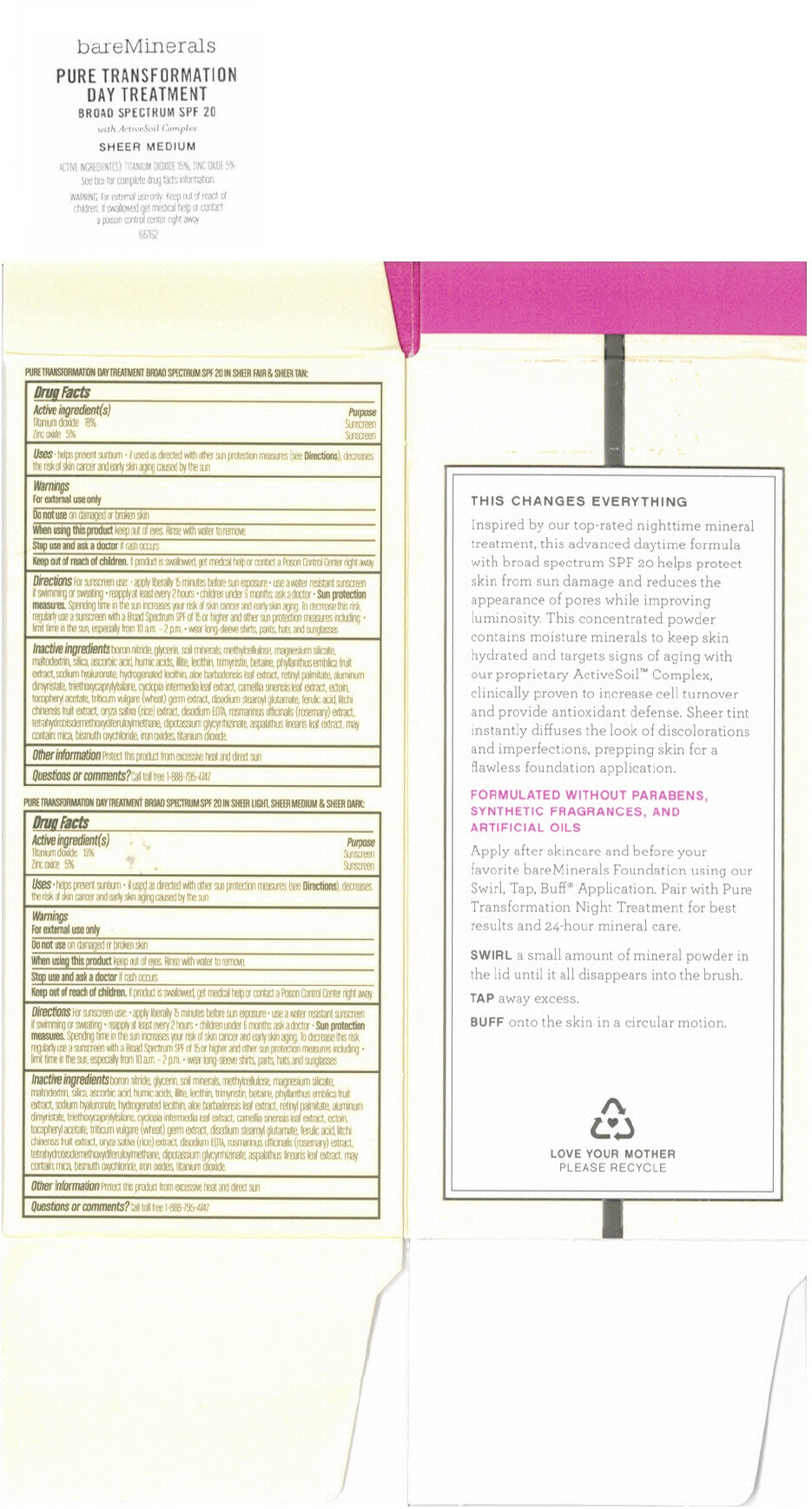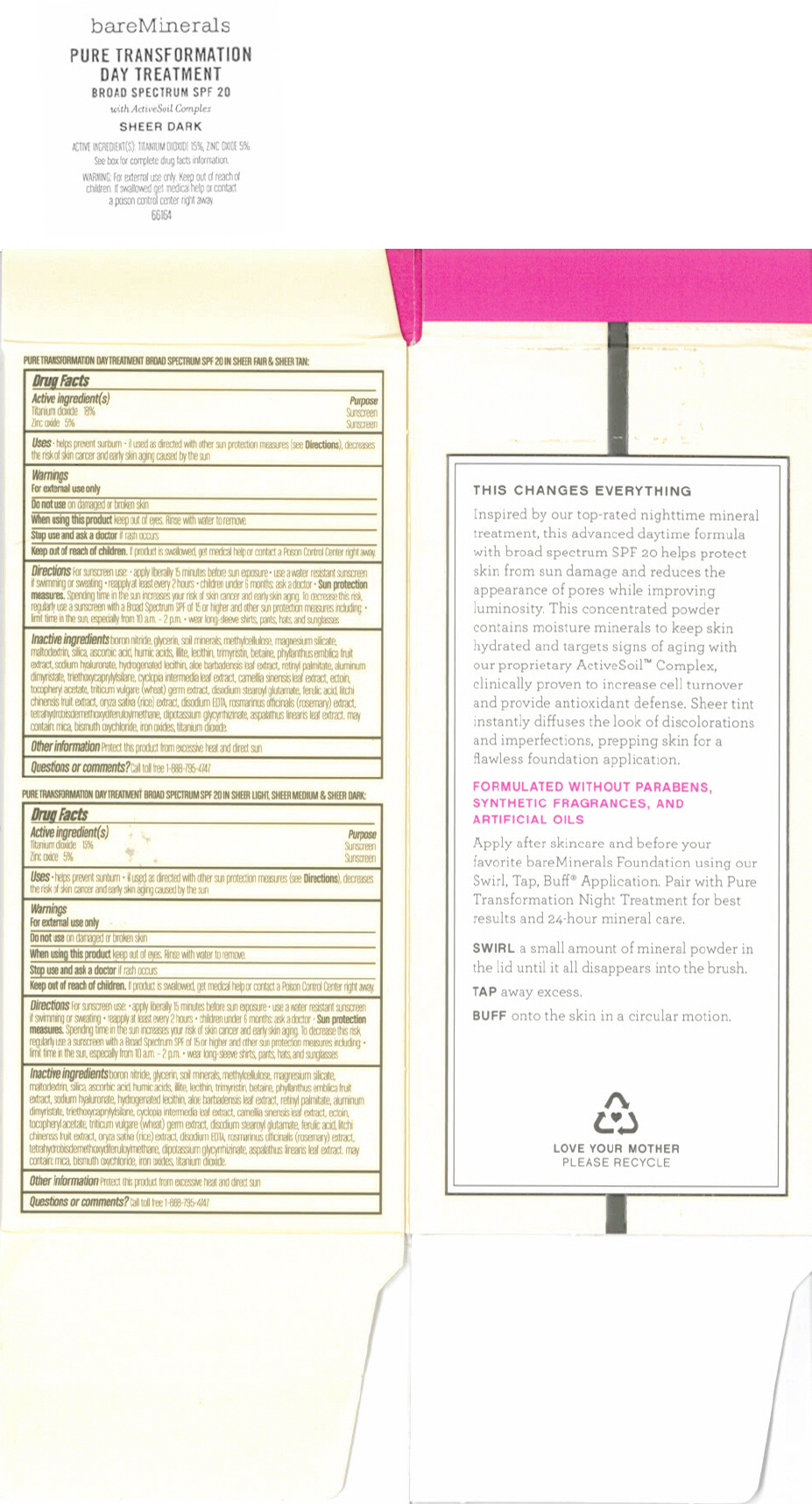 DRUG LABEL: Pure Transformation Sheer Light
NDC: 98132-187 | Form: POWDER
Manufacturer: Bare Escentuals Beauty Inc.
Category: otc | Type: HUMAN OTC DRUG LABEL
Date: 20130916

ACTIVE INGREDIENTS: Titanium Dioxide 15 g/100 g; Zinc Oxide 5 g/100 g
INACTIVE INGREDIENTS: boron nitride; glycerin; CARBOXYMETHYLCELLULOSE; magnesium silicate; maltodextrin; silicon dioxide; ascorbic acid; EGG PHOSPHOLIPIDS; TRIMYRISTIN; betaine; PHYLLANTHUS EMBLICA FRUIT; hyaluronate sodium; aloe; VITAMIN A PALMITATE; ALUMINUM DIMYRISTATE; triethoxycaprylylsilane; CYCLOPIA INTERMEDIA LEAF; GREEN TEA LEAF; ectoine; .alpha.-tocopherol acetate; WHEAT GERM; disodium stearoyl glutamate; ferulic acid; LITCHI FRUIT; RICE GERM; Edetate Disodium; rosemary; TETRAHYDROBISDEMETHOXYDIFERULOYLMETHANE; glycyrrhizinate dipotassium; aspalathus linearis leaf; mica; BISMUTH OXYCHLORIDE; FERRIC OXIDE RED

Pure Transformation Day Treatment Broad Spectrum SPF 20 in Light (Medium or Dark)

Drug Facts

Active Ingredients

Titanium Dioxide 15% Purpose: Sunscreen
Zinc oxide 5% Purpose: Sunscreen

Uses

Helps prevent sunburn. If used as directed with other sun protection measures (see Directions), decreases the risk of skin cancer and early skin aging caused by the sun.

Warnings

For external use only

Do not use on damaged or broken skin.

When using this product: Keep out of Eyes ; Rinse with water to remove

Stop use and ask a doctor if rash occurs.

Keep out of reach of children. If swallowed, get medical help or contact a Poison Control Center right away.

Directions

For sunscreen use

Apply liberally 15 minutes before sun exposure

Use a water resistant sunscreen if swimming or sweating

Reapply at least every 2 hours

Children under 6 months, ask a doctor.

Sun protection measures

Spending time in the sun increases your risk of skin cancer and early skin aging. To decrease this risk, regularly use a sunscreen with a Broad Spectrum SPF of 15 or higher and other sun protection measures including: limit time in the sun, especially from 10am to 2 pm, wear long-sleeve shirts, pants, hats, and sunglasses.

Inactive Ingredients

Boron nitride, glycerin, methylcellulose, maltodextrin, ascorbic acid, illite, trimyrstintin, betaine, phylantus embilica frut extract, sodium hyaluronate, hydrogenated lecithin, aloe barbensis leaf extract, retintyl palmitate, aluminum dimyristate, triethoxycaprylsilane, cyclopia intermedia leaf extract, cameria sinensis leaf extract, ectoin, tocopheryl acetate, triticum vulgare (wheat germ extract), disodium stearoyl glutamate, ferulic acid, litchi chinesis fruit extract, oryza sativa (rice) extract, disodium EDTA, rosmarinus officinalis (rosemary) extract, tetrahydrobisdemthoxydiferuloylmethane, dipotassium glycyrrhizinate, aspalathus linearis leaf extract. May contain: mica. bismuth oxychloride, titanium dioxide, iron oxides.

Other information

Protect this product from excessive heat and direct sun

Questions or comments?

Call toll free 1-888-795-4747

Bare Escentuals
MADE IN USA
Distr. By Bare Escentuals Beauty Inc., San Francisco CA 94104 USA
London W10 3QB

PRINCIPAL DISPLAY PANEL - Jar Label - SHEER LIGHT

bareMinerals

PURE TRANSFORMATION
DAY TREATMENT
BROAD SPECTRUM SPF 20
with ActiveSoil Complex

SHEER LIGHT

ACTIVE INGREDIENT(S): TITANIUM DIOXIDE 15%, ZINC OXIDE 5%

See box for complete drug facts information.

WARNING: For external use only. Keep out of reach of
children. If swallowed get medical help or contact
a poison control center right away.

66161

PRINCIPAL DISPLAY PANEL - Jar Label - SHEER MEDIUM

bareMinerals

PURE TRANSFORMATION
DAY TREATMENT
BROAD SPECTRUM SPF 20
with ActiveSoil Complex

SHEER MEDIUM

ACTIVE INGREDIENT(S): TITANIUM DIOXIDE 15%, ZINC OXIDE 5%

See box for complete drug facts information.

WARNING: For external use only. Keep out of reach of
children. If swallowed get medical help or contact
a poison control center right away.

66162

PRINCIPAL DISPLAY PANEL - Jar Label - SHEER DARK

bareMinerals

PURE TRANSFORMATION
DAY TREATMENT
BROAD SPECTRUM SPF 20
with ActiveSoil Complex

SHEER DARK

ACTIVE INGREDIENT(S): TITANIUM DIOXIDE 15%, ZINC OXIDE 5%

See box for complete drug facts information.

WARNING: For external use only. Keep out of reach of
children. If swallowed get medical help or contact
a poison control center right away.

66164